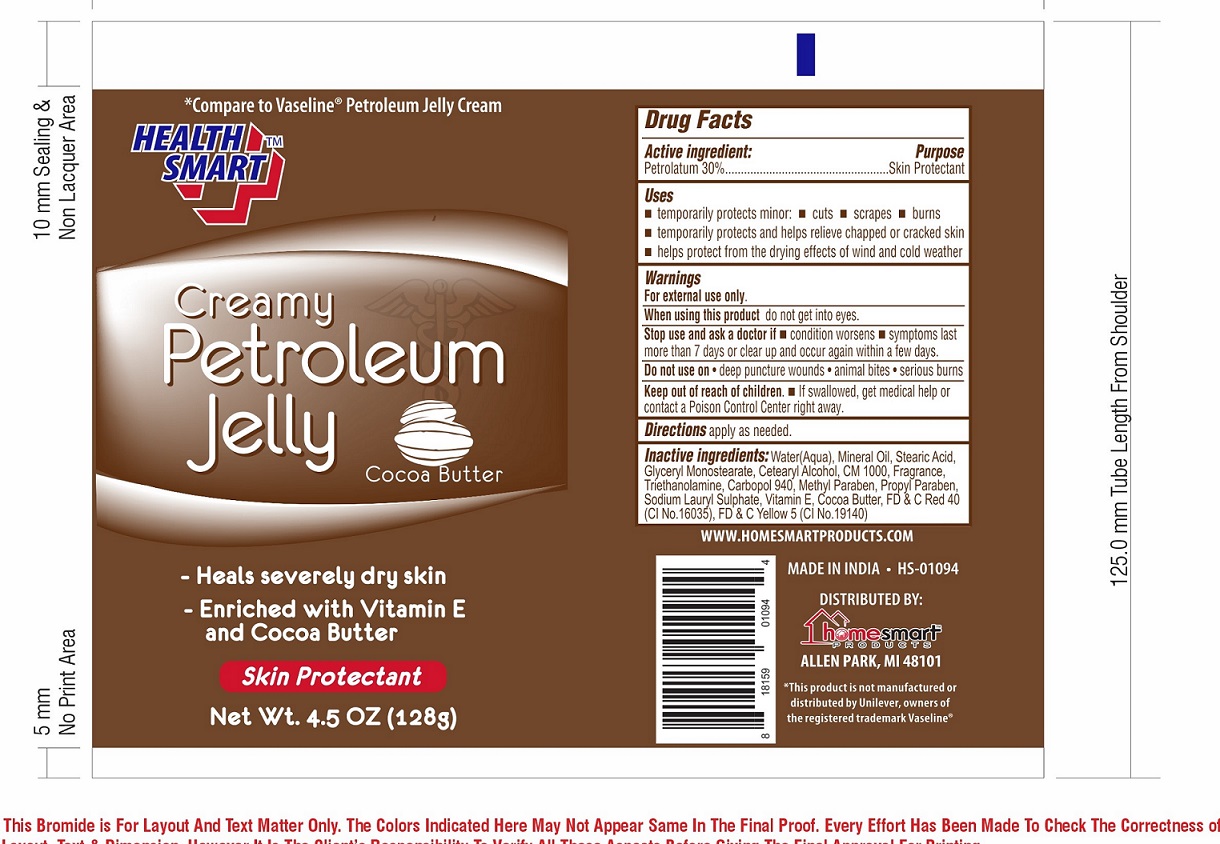 DRUG LABEL: Petroleum Jelly Cocoa Butter
NDC: 73398-113 | Form: CREAM
Manufacturer: SUHAN AEROSOL
Category: otc | Type: HUMAN OTC DRUG LABEL
Date: 20201026

ACTIVE INGREDIENTS: PETROLATUM 30 g/100 g
INACTIVE INGREDIENTS: WATER; MINERAL OIL; STEARIC ACID; GLYCERYL MONOSTEARATE; CETOSTEARYL ALCOHOL; CETETH-20; TROLAMINE; CARBOMER HOMOPOLYMER TYPE C (ALLYL PENTAERYTHRITOL CROSSLINKED); METHYLPARABEN; PROPYLPARABEN; SODIUM LAURYL SULFATE; .ALPHA.-TOCOPHEROL; COCOA BUTTER; FD&C RED NO. 40; FD&C YELLOW NO. 5

Health Smart Creamy Petroleum Jelly –Cocoa Butter

Active Ingredient

Petrolatum 30%

Purpose

Skin Protectant

Uses

- Temporarily protects minor cuts ,scrapes, and burns.
- Temporarily protects and helps relieve chapped or cracked skin.
- Helps protect from the drying effects of wind and cold weather.

Warnings

- For external use only.
- When using this product do not get into eyes.
- Stop use and ask a doctor if condition worsens,symptoms last more than 7 days or clear up and occur again within a few days.
- Do not use on deep puncture wounds.If swallowed,get medical help or contact a poison control center right away

Keep Out of reach of children

If swallowed, get medical help or contact Poison Control Center right away.

Directions

Apply as needed.

Inactive ingredients

Water,Mineral Oil,Stearic Acid,Glyceryl Monostearate,Cetearyl Alcohol,CM 1000,Fragrance,Triethanolamine,Carbopol 940,Methyl Paraben,
Propyl Paraben,Sodium Lauryl Sulphate,Vitamin E,Cocoa Butter,FD and C Red 40[CI No.16035],FD and C Yellow 5 [CI No .19140].